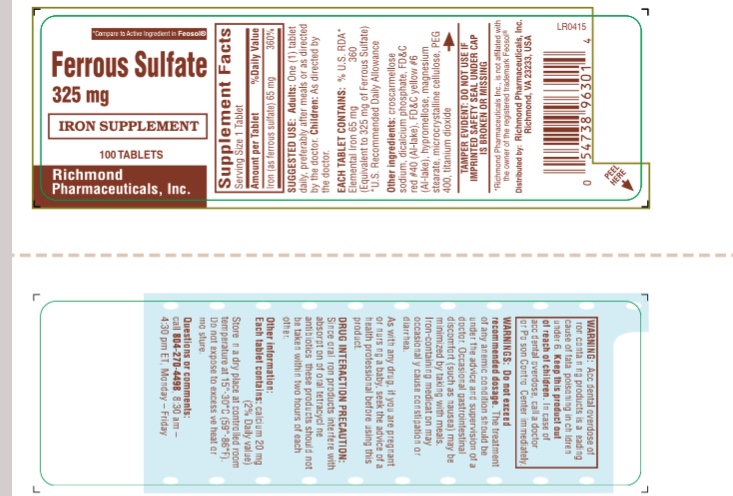 DRUG LABEL: FERROUS SULFATE
NDC: 54738-963 | Form: TABLET
Manufacturer: Richmond Pharmaceuticals, Inc.
Category: otc | Type: HUMAN OTC DRUG LABEL
Date: 20241226

ACTIVE INGREDIENTS: FERROUS SULFATE 325 mg/1 1
INACTIVE INGREDIENTS: CROSCARMELLOSE SODIUM; DIBASIC CALCIUM PHOSPHATE DIHYDRATE; FD&C RED NO. 40; FD&C YELLOW NO. 6; HYPROMELLOSES; MAGNESIUM STEARATE; CELLULOSE, MICROCRYSTALLINE; POLYETHYLENE GLYCOL 400; TITANIUM DIOXIDE

FERROUS SULFATE TABLETS 325 mg

Supplement Facts[/S]

Serving Size: 1 Tablet Amount per Tablet | % Daily Value
Iron (as ferrous sulfate) 65 mg | 360 %

SUGGESTED USE

Adults:One (1) tablet daily, preferably after meals or as directed by the doctor. Children:As directed by the doctor.

Active Ingredient

EACH TABLET CONTAINS: %U.S. RDA*

Elemental Iron 65 mg 360

(Equivalent to 325 mg of Ferrous Sulfate)

* U.S. Recommended Daily Allowance

Inactive Ingredients

Croscarmellose sodium, dicalcium phosphate, FD&C RED#40 (Al-lake), FD&C yellow #6 (Al-lake), hypromellose, magnesium stearate, microcrystalline cellulose, PEG 400, titanium dioxide

Purpose

Iron Supplement

WARNING:

Accidental overdose of iron containing products is a leading cause of fatal poisoning in children under 6. Keep this product out of reach of children. In case of accidental overdose, call a doctor or Poison Control Center immediately.

WARNINGS: Do not exceed recommended dosage.The treatment of any anemic condition should be under the advice and supervision of doctor. Occasional gastrointestinal discomfort (such as nausea) may be minimized by taking with meals. Iron-containing medication may occasionally cause constipation or diarrhea.

As with any drug, if you are pregnant or nursing baby, seek the advice of a health professional before using this product.

DRUG INTERACTION PRECAUTION

Since oral iron products interfere with absorption of oral tetracycline antibiotics , these products should not be taken within two hours of each other.

DOSAGE AND ADMINISTRATION

Each tablet contains:Calcium 20 mg (2% daily value) Store in a dry place at controlled room temperature at 15-30 °C (59°-86° F). Do not expose to excessive heat or moisture.

Questions or Comments

DO NOT USE IF IMPRINTED SAFETY SEAL UNDER CAP IS MISSING OR DAMAGED

Call 804-270-4498 Monday-Friday, 8.30 am – 4.30 pm ET

Package Label

FERROUS SULFATE TABLETS 325 mg (5 gr)

Iron Supplement

NDC: 54738-963-01 – 100 Tablets

NDC: 54738-963-03 – 1000 TABLETS